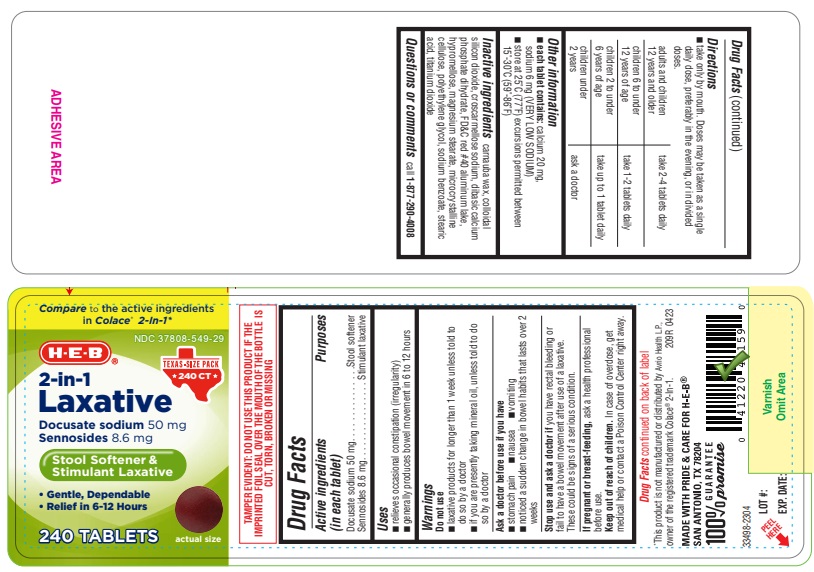 DRUG LABEL: Stool Softener and Stimulant Laxative
NDC: 37808-549 | Form: TABLET
Manufacturer: H-E-B
Category: otc | Type: HUMAN OTC DRUG LABEL
Date: 20250214

ACTIVE INGREDIENTS: DOCUSATE SODIUM 50 mg/1 1; SENNOSIDES 8.6 mg/1 1
INACTIVE INGREDIENTS: SILICON DIOXIDE; HYPROMELLOSES; MAGNESIUM STEARATE; POLYETHYLENE GLYCOL, UNSPECIFIED; CARNAUBA WAX; TITANIUM DIOXIDE; SODIUM BENZOATE; MICROCRYSTALLINE CELLULOSE; CROSCARMELLOSE SODIUM; DIBASIC CALCIUM PHOSPHATE DIHYDRATE; FD&C RED NO. 40 ALUMINUM LAKE; STEARIC ACID

HEB 209R Sennosides 8.6mg / Docusate Sodium 50mg 240ct

Drug Facts

Active ingredients (in each tablet)

Docusate sodium 50 mg

Sennosides 8.6 mg

Purposes

Stool Softener

Stimulant laxative

USES

- relieves occasional constipation (irregularity)
- generally produces bowel movement in 6 to 12 hours

Warnings

Do not use

- laxative products for longer than 1 week unless told to do so by a doctor
- if you are presently taking mineral oil unless told to do so by a doctor

Ask a doctor before use if you have

- stomach pain
- nausea
- vomiting
- noticed a sudden change in bowel habits that lasts over 2 weeks

Stop use and ask a doctor if you have rectal bleeding or fail to have a bowel movement after use of a laxative. These could be signs of a serious condition.

PREGNANCY OR BREAST FEEDING

If pregnant or breast-feeding, ask a health professional before use.

Keep out of reach of children. In case of overdose, get medical help or contact a Poison Control Center right away (1-800-222-1222).

Directions

- take only by mouth. Doses may be taken as a single daily dose, preferably in the evening, or in divided doses.

adults and children; 12 years and older | take 2-4 tablets daily
children 6 to; under 12 years of age | take 1-2 tablets daily
children 2 to; under 6 years of age | take up to 1 tablet daily
children under 2 | ask a doctor

Other information

- each tablet contains: calcium 20 mg, sodium 6 mg (VERY LOW SODIUM)
- Store at 25°C (77°F) excursions permitted between 15°-30°C (59°-86°F)

INACTIVE INGREDIENT

Inactive ingredients carnauba wax, colloidal silicon dioxide, croscarmellose sodium, dibasic calcium phosphate dihydrate, FD&C red #40 aluminum lake, hypromellose, magnesium stearate, microcrystalline cellulose, polyethylene glycol, sodium benzoate, stearic acid, titanium dioxide

Questions or comments call 1-877-290-4008